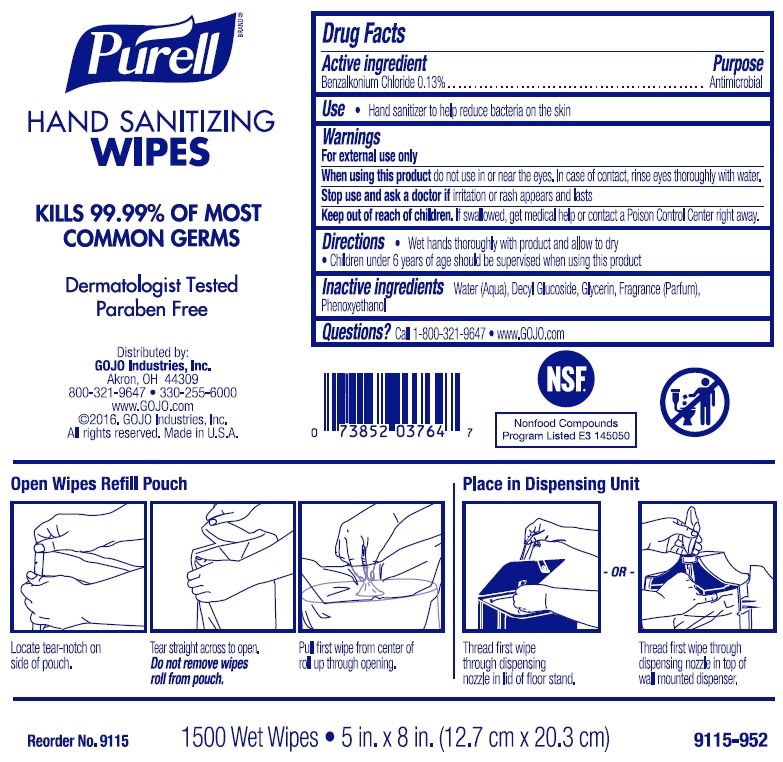 DRUG LABEL: PURELL Hand Sanitizing Wipes
NDC: 21749-368 | Form: CLOTH
Manufacturer: GOJO Industries, Inc.
Category: otc | Type: HUMAN OTC DRUG LABEL
Date: 20241212

ACTIVE INGREDIENTS: BENZALKONIUM CHLORIDE 0.13 mg/100 mL
INACTIVE INGREDIENTS: WATER; DECYL GLUCOSIDE; GLYCERIN; PHENOXYETHANOL

PURELL Hand Sanitizing Wipes

Active ingredient

Benzalkonium Chloride 0.13%

Purpose

Antimicrobial

Uses

- Hand sanitizer to help reduce bacteria on the skin

Warnings

For external use only

When using this product do not use in or near the eyes. In case of contact, rinse eyes thoroughly with water.

Stop use and ask a doctor if irritation or rash appears and lasts

Keep Out of Reach of Children. If swallowed, get medical help or contact a Poison Control Center right away.

Directions

- Wet hands thoroughly with product and allow to dry
- Children under 6 years of age should be supervised when using PURELL

Inactive ingredients

Water (Aqua), Decyl Glucoside, Glycerin, Fragrance(Parfum), Phenoxyethanol